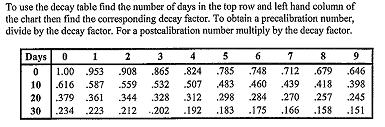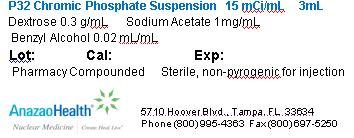 DRUG LABEL: P32 Sodium Phosphate
NDC: 51808-127 | Form: INJECTION, SUSPENSION
Manufacturer: AnazaoHealth Corporation
Category: prescription | Type: HUMAN PRESCRIPTION DRUG LABEL
Date: 20120619

ACTIVE INGREDIENTS: PHOSPHORUS P-32 5 mCi/1 mL
INACTIVE INGREDIENTS: DEXTROSE 0.3 g/1 mL; BENZYL ALCOHOL 0.02 mL/1 mL; SODIUM ACETATE 1 mg/1 mL

P32 Chromic Phosphate Suspension

DESCRIPTION

AnazaoHealth’s compounded P32 Chromic Phosphate is supplied as a sterile, nonpyrogenic aqueous solution. It contains 30 % dextrose solution, 1 mg sodium acetate, 2 % benzyl alcohol added as a preservative. Sodium hydroxide or hydrochloric acid may be added for pH adjustment.

INDICATIONS AND USAGE

P32 chromic phosphate is indicated for intracavitary instillation for the treatment of peritoneal or pleural effusions caused by metastatic disease, and may be injected interstitially for the treatment of cancer. It is also used in hemophilia patients for intraarticular injections.

Mechanism of Action

Radioactive phosphorous works by local irradiation by beta emission.

CONTRAINDICATIONS

P32 sodium phosphate should not be used in the presence of ulcerative tumors.

WARNINGS

Not for intravascular injection.

DOSAGE AND ADMINISTRATION

Shake the vial well before injection.

For intraperitoneal instillation, administer 10-20 mCi

For intrapleural instillation, administer 6 to 12 mCi

Doses for interstitial use should be based on estimated gram weight of tumor, about 0.1 to 0.5 mCi/gm.

PACKAGE LABEL.PRINCIPAL DISPLAY PANEL

Figure 1